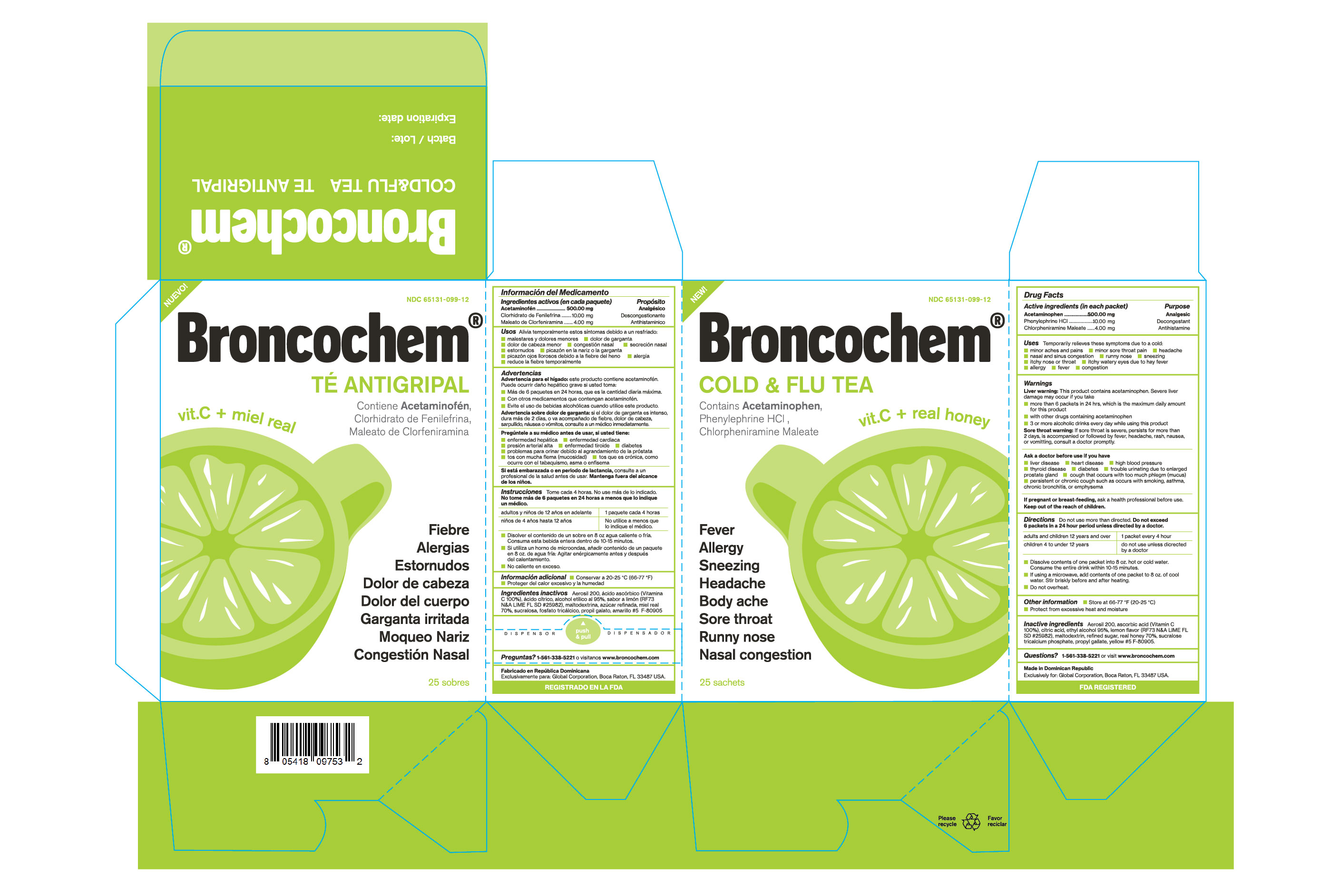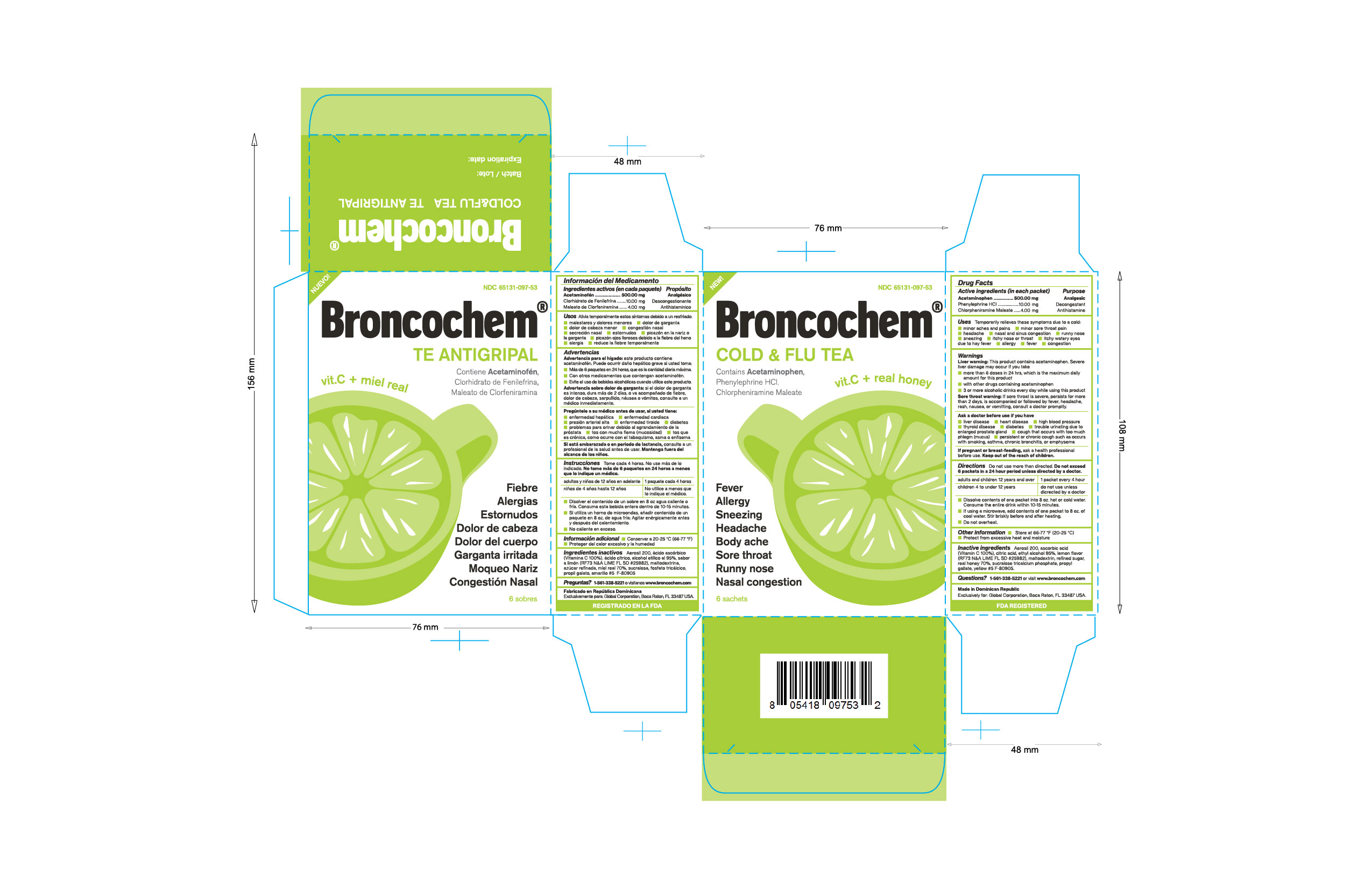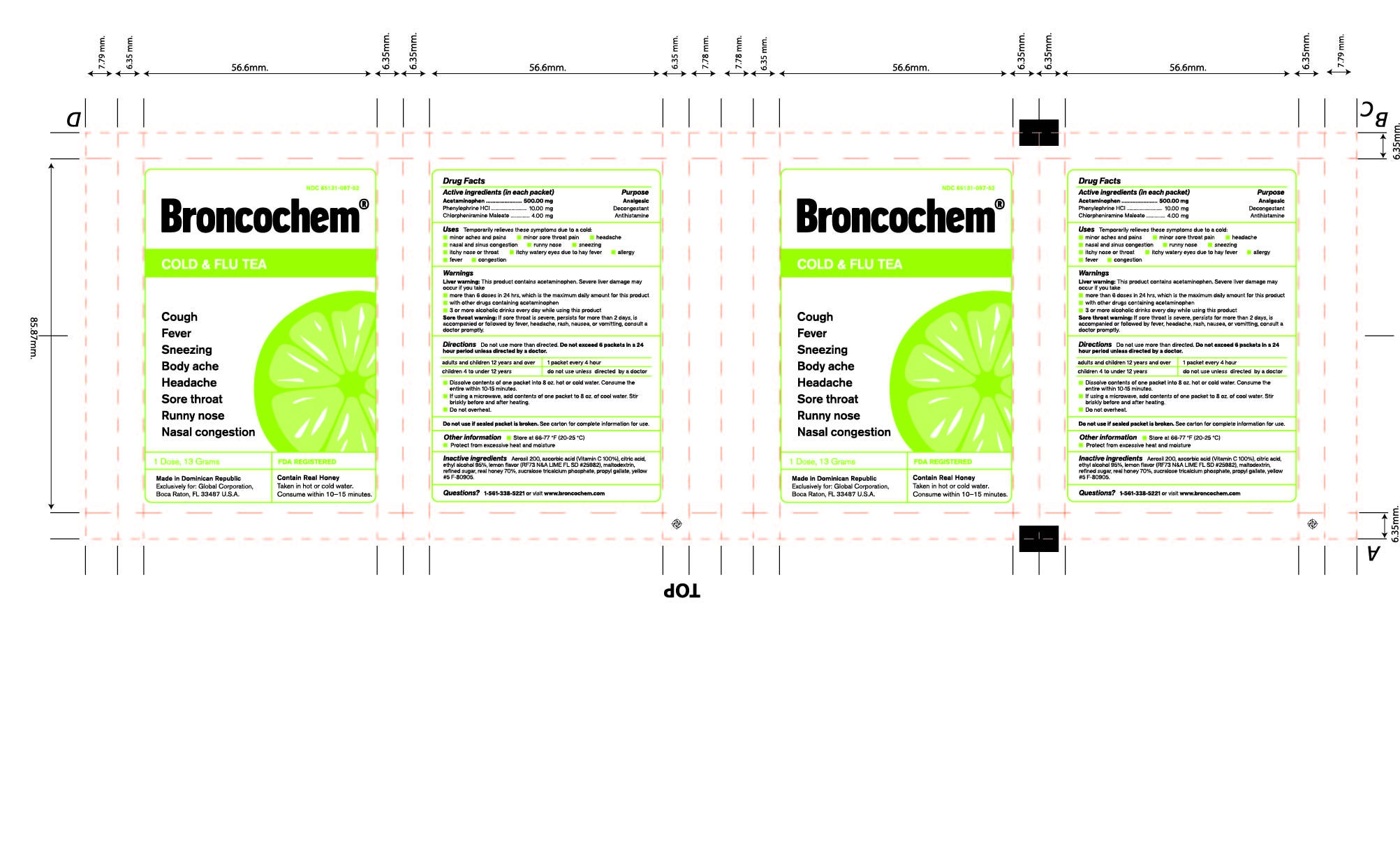 DRUG LABEL: BRONCOCHEM
NDC: 65131-097 | Form: GRANULE, FOR SOLUTION
Manufacturer: LABORATORIO MAGNACHEM INTERNATIONAL SRL
Category: otc | Type: HUMAN OTC DRUG LABEL
Date: 20241212

ACTIVE INGREDIENTS: ACETAMINOPHEN 500 mg/13 g; CHLORPHENIRAMINE MALEATE 4 mg/13 g
INACTIVE INGREDIENTS: PHENYLEPHRINE HYDROCHLORIDE 10 mg/13 g; ASCORBIC ACID 66 mg/13 g; SUCROSE 9483 mg/13 g; CITRIC ACID MONOHYDRATE 1500 mg/13 g; HONEY 100 mg/13 g; MALTODEXTRIN 1000 mg/13 g; TRICALCIUM PHOSPHATE 166.6 mg/13 g; SUCRALOSE 28.43 mg/13 g; SILICON DIOXIDE 40 mg/13 g; PROPYL GALLATE 0.433 mg/13 g; ALCOHOL 0.001 mL/13 g

BRONCOCHEM COLD AND FLU TEA

Warnings

Liver warning:

This product contains acetaminophen, severe liver damage may occur if you take:

- More than 6 packets in 24 hours, which is the maximum daily amount.
- with other drugs containing acetaminophen.
- three (3) or more alcoholic drinks every day while using this product.

Sore Tthroat warning:

If sore throat is severe, persists for more than 2 days, is accompainied or followed by fever, headache, rash, nausea or vomiting consult a doctor promptly.

Active Ingredients

Acetaminophen.

Phenylephrine Hydrochloride.

Chlorpheniramine Maleate

Purpose

Pain reliever/fever reducer

Nasal decongestant

Antihistamine

Keep Out of the Reach of Children

In case of overdose get medical help or contact a Poison Control Center right away, prompt medical attention is critical for adults as well as for children even if you do not notice any signs symptoms.

Indications and Usage

Temporarily relieves these symptoms due to a cold:

- Minor aches and pains.
- Minor sore throat pain.
- Headache.
- Nasal and sinus congestion.
- Runny nose.
- Sneezing
- Itchy nose or throat.
- Itchy, watery eyes due to hay fever.
- Cough due to minor throat and bronchial irritation.
- Temporarily reduces fever.

Dosage and Administration

Do not use more than directed.

Take every 4 hours; do not take more than 6 packets in 24 hours unless directed by a doctor.

Children under 4 years of age-Do not ue.

Children from 4 to 12 years of age-Do not use unless directed by a doctor.

Adults and children 12 years of age and over-One packet

Dissolve contents of one packet into 8 oz of hot or cold water, consume entire drink within 10-15 minutes.

If using a microwave, add contents of one packet to 8 oz of cool wter stir briskly before and after heating.

Do not over heat.

Inactive Ingredients

Ascorbic acid, Silicon Dioxide, Citric Acid Monohydrate, Ethyl alcohol, Lime flavor, Maltodextrin, Sucrose, Honey, Sucralose, Tricalcium phosphate, Propyl gallate, Yellow No.5